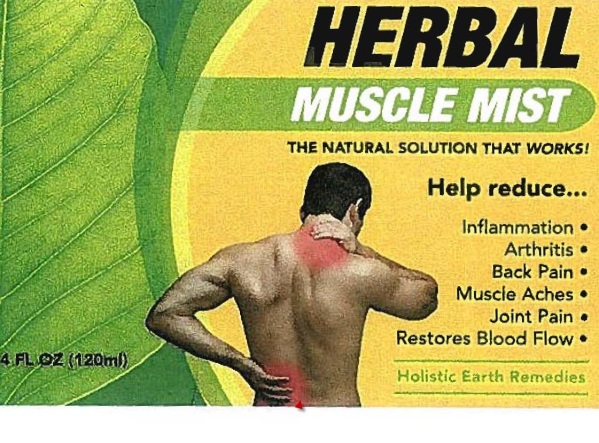 DRUG LABEL: Muscle Mist
NDC: 69257-110 | Form: SOLUTION
Manufacturer: Signature Formulations LLC
Category: otc | Type: HUMAN OTC DRUG LABEL
Date: 20141103

ACTIVE INGREDIENTS: MENTHOL 6 g/100 mL; CAMPHOR (SYNTHETIC) 2 g/100 mL
INACTIVE INGREDIENTS: ISOPROPYL ALCOHOL; EUCALYPTUS OIL; METHYL SALICYLATE; PEPPERMINT OIL; CLOVE OIL

Muscle Mist

Active ingredient

Menthol USP 6%
Camphor 2%

Purpose

Pain Relief

Other ingredients

The Isopropyl Alcohol, Camphor Powder, Eucalyptus, Globulus Leaf Oil, Sweet Birch Oil, Peppermint Oil, Clove Bud Oil

Uses

For the temporary relief of minor aches and pains at muscles and joints associated with sore muscles, strains, joint discomfort and arthritis

Warnings

For external use only. Avoid contact with eyes. Do not apply to wounds or damaged skin. If pregnant or breast feeding ask a health care professional before use. Keep out of reach of children. If swallowed get medical help or contact a poison control center. Flammable: Keep away from fire or flame.

Directions

Adults and children over 12 years. Spray onto neck and shoulders to help relieve tension and stress. Rub into temples to help with headaches. Spray onto chest to help relieve cold and flu. Apply prior to a workout or sports activity

Manufactured for:

Holistic Earth Remedies
Phoenix, Arizona 602.300.3691
holisticearthremedies.com

Package/Label Principal Display Panel

HERBAL
MUSCLE MIST

THE NATURAL SOLUTION THAT WORKS!

Help reduce…

Inflammation ●
Arthritis ●
Back Pain ●
Muscle Aches ●
Joint Pain ●
Restores Blood Flow ●

Holistic Earth Remedies

4 FL OZ (120ml)

Carton Label